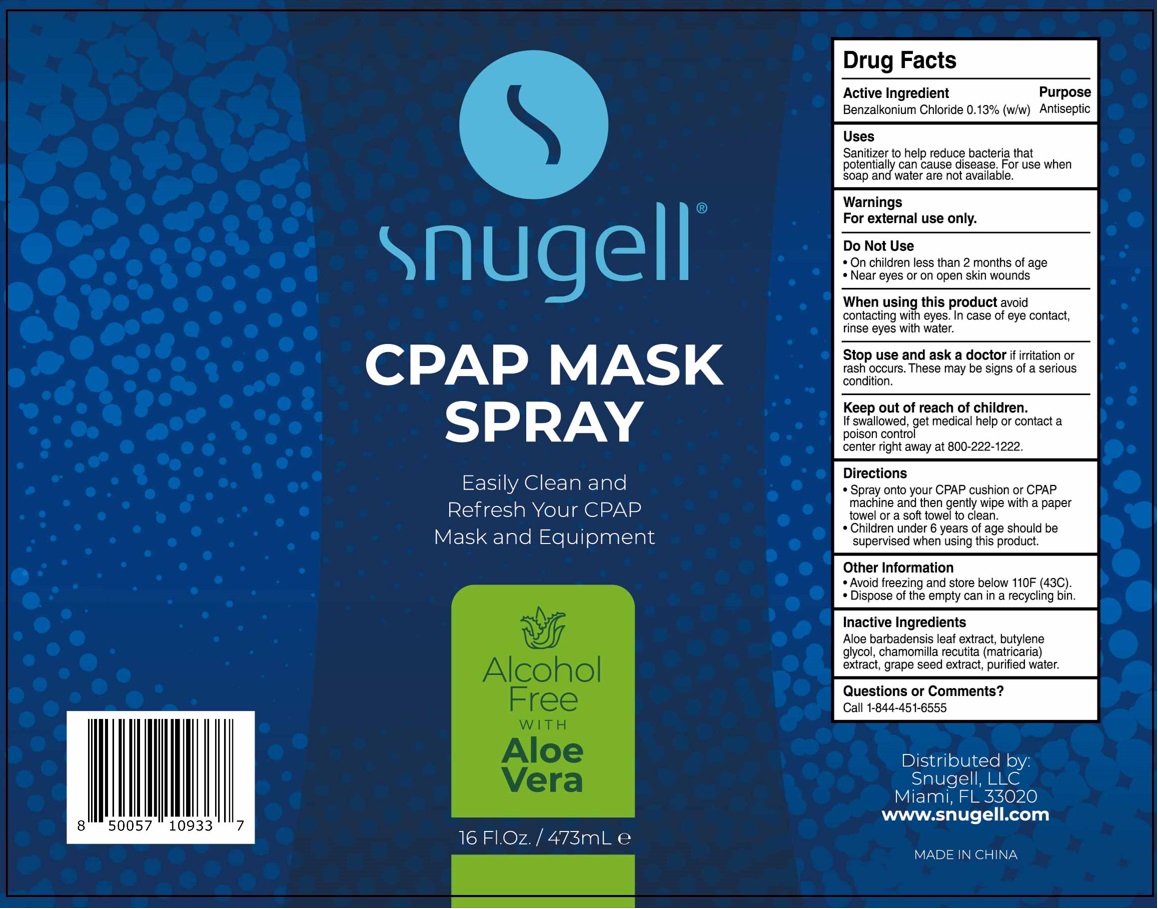 DRUG LABEL: Snugell
NDC: 80671-005 | Form: SPRAY
Manufacturer: QUANZHOU AIWINA HYGIENE PRODUCTS CO.,LTD
Category: otc | Type: HUMAN OTC DRUG LABEL
Date: 20241217

ACTIVE INGREDIENTS: BENZALKONIUM CHLORIDE 0.13 g/100 mL
INACTIVE INGREDIENTS: ALOE VERA LEAF; BUTYLENE GLYCOL; MATRICARIA CHAMOMILLA WHOLE; VITIS VINIFERA SEED; WATER

snugell® CPAP MASK SPRAY

Active Ingredient

Benzalkonium Chloride 0.13% (w/w)

Purpose

Antiseptic

Uses

Sanitizer to help reduce bacteria that potentially can cause disease. For use when soap and water are not available.

Warnings

For external use only.

Do Not Use
• On children less than 2 months of age
• Near eyes or on open skin wounds

When using this product avoid contacting with eyes. In case of eye contact, rinse eyes with water.

Stop use and ask a doctor if irritation or rash occurs. These may be signs of a serious condition.

Keep out of reach of children. If swallowed, get medical help or contact a poison control center right away at 800-222-1222.

Directions

• Spray onto your CPAP cushion or CPAP machine and then gently wipe with a paper towel or a soft towel to clean.
• Children under 6 years of age should be supervised when using this product.

Other Information

• Avoid freezing and store below 110F (43C).
• Dispose of the empty can in a recycling bin.

Inactive Ingredients

Aloe barbadensis leaf extract, butylene glycol, chamomilla recutita (matricaria) extract, grape seed extract, purified water.

Questions or Comments?

Call 1-844-451-6555

Easily Clean and Refresh Your CPAP Mask and Equipment

Alcohol Free
WITH
Aloe Vera

Distributed by:
Snugell, LLC
Miami, FL 33015
www.snugell.com

MADE IN CHINA